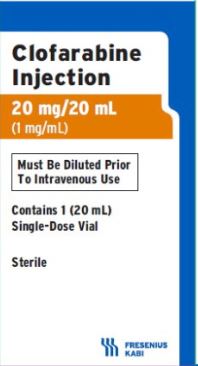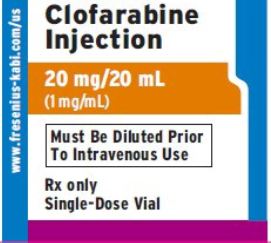 DRUG LABEL: CLOFARABINE
NDC: 49315-003 | Form: INJECTION
Manufacturer: Zydus Lifesciences Limited
Category: prescription | Type: HUMAN PRESCRIPTION DRUG LABEL
Date: 20221018

ACTIVE INGREDIENTS: CLOFARABINE 1 mg/1 mL
INACTIVE INGREDIENTS: SODIUM CHLORIDE 9 mg/1 mL; WATER

Clofarabine Injection, for Intravenous use

PACKAGE LABEL.PRINCIPAL DISPLAY PANEL

NDC 49315-003-06

Rx only

Clofarabine Injection 20 mg/20 mL (1 mg/mL)

Must Be Diluted Prior To Intravenous Use

Contains 1 (20 mL) Single-Dose Vial

Sterile

PACKAGE LABEL.PRINCIPAL DISPLAY PANEL

NDC 49315-003-06

Clofarabine Injection 20 mg/20 mL (1 mg/mL)

Must Be Diluted Prior To Intravenous Use

Rx only Single-Dose Vial